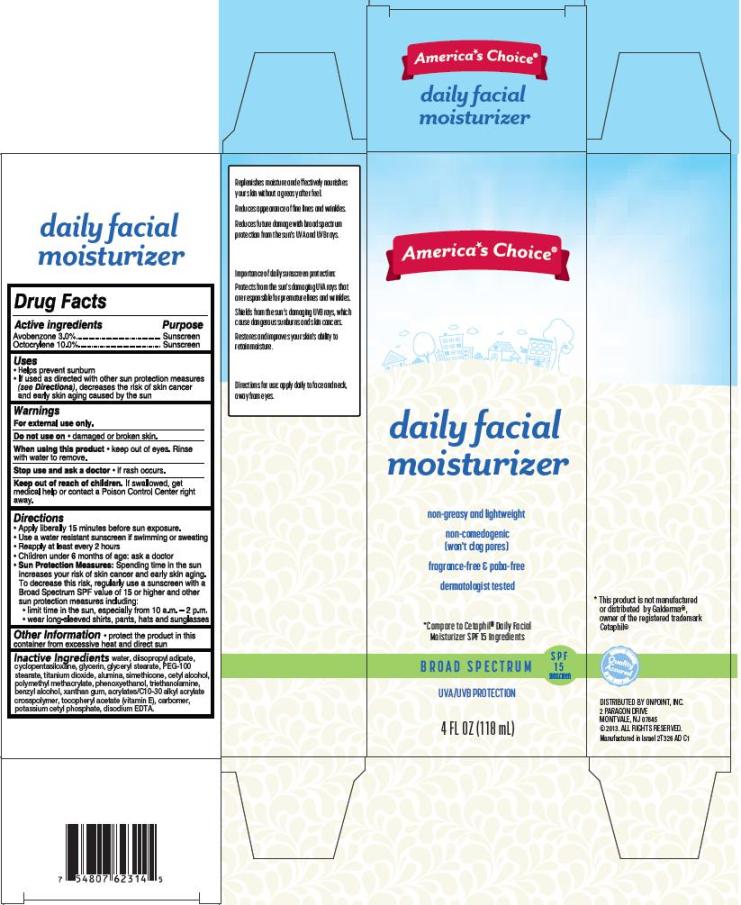 DRUG LABEL: Daily Facial Moisturizer Broad Spectrum SPF15 Sunscreen
NDC: 42421-326 | Form: CREAM
Manufacturer: Emilia Personal Care Inc.
Category: otc | Type: HUMAN OTC DRUG LABEL
Date: 20140109

ACTIVE INGREDIENTS: AVOBENZONE 3 g/100 mL; OCTOCRYLENE 10 g/100 mL
INACTIVE INGREDIENTS: WATER; DIISOPROPYL ADIPATE; CYCLOMETHICONE 5; GLYCERIN; GLYCERYL 1-STEARATE; PEG-100 STEARATE; TITANIUM DIOXIDE; ALUMINUM OXIDE; SILICON DIOXIDE; CETYL ALCOHOL; POLY(METHYL ACRYLATE-CO-METHYL METHACRYLATE-CO-METHACRYLIC ACID 7:3:1; 280000 MW); PHENOXYETHANOL; TROLAMINE; BENZYL ALCOHOL; XANTHAN GUM; CARBOMER COPOLYMER TYPE A (ALLYL PENTAERYTHRITOL CROSSLINKED); .ALPHA.-TOCOPHEROL ACETATE; POTASSIUM CETYL PHOSPHATE; EDETATE DISODIUM

America's Choice® daily facial moisturizer

Active ingredients

Avobenzone 3.0%

Octocrylene 10.0%

Purpose

Sunscreen

Uses

- Helps prevent sunburn
- If used as directed with other sun protection measures (see Directions), decreases the risk of skin cancer and early skin aging caused by the sun

Warnings

For external use only.

Do not use on damaged or broken skin.

When using this product keep out of eyes. Rinse with water to remove.

Stop use and ask a doctor if rash occurs.

Keep out of reach of children

If swallowed, get medical help or contact a Poison Control Center right away.

Directions

Apply liberally 15 minutes before sun exposure.

Use a water resistant sunscreen if swimming or sweating

Reapply at least every 2 hours

Children under 6 months of age: ask a doctor

Sun Protection Measures: Spending time in the sun increases your risk of skin cancer and early skin aging. To decrease this risk, regularly use a sunscreen with a Broad Spectrum SPF value of 15 or higher and other sun protection measures including:

- limit time in the sun, especially from 10 a.m.-2 p.m.
- wear long-sleeved shirts, pants, hats and sunglasses

Other Information

- protect the product in this container from excessive heat and direct sun

Inactive ingredients

water, diisopropyl adipate, cyclopentasiloxane, glycerin, glyceryl stearate, PEG-100 stearate, titanium dioxide, alumina, simethicone, cetyl alcohol, polymethyl methacrylate, phenoxyethanol, triethanolamine, benzyl alcohol, xanthan gum, acrylates/C10-30 alkyl acrylate crosspolymer, tocopheryl acetate (vitamin E), carbomer, potassium cetyl phosphate, disodium EDTA.

Package/Label Principal Display Panel

America's Choice® daily facial moisturizer

non-greasy and lightweight

non-comedogenic

(won't clog pores)

fragrance-free & paba-free

dermatologist tested

*Compare to Cetaphil® Daily Facial Moisturizer SPF 15 ingredients

BROAD SPECTRUM SPF15 SUNSCREEN

UVA/UVB PROTECTION

4 FL OZ (118 mL)

*This product is not manufactured or distributed by Galderma®, owner of the registered trademark Cetaphil®

DISTRIBUTED BY ONPOINT, INC.
2 PARAGON DRIVE
MONTVALE, NJ 07645

Manufactured in Israel 2T326 AD C1

Carton Label